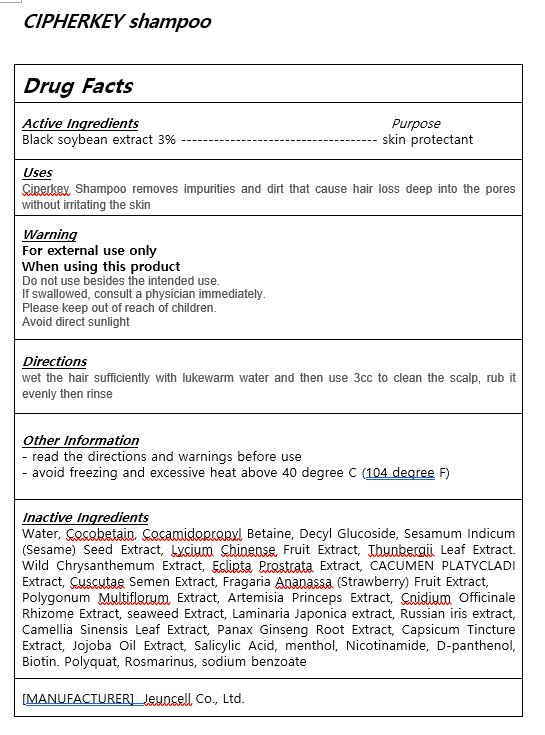 DRUG LABEL: CIPHERKEYshampoo
NDC: 54296-0001 | Form: SHAMPOO
Manufacturer: Jeuncell Co.,Ltd
Category: otc | Type: HUMAN OTC DRUG LABEL
Date: 20230921

ACTIVE INGREDIENTS: SOYBEAN OIL 3 g/100 mL
INACTIVE INGREDIENTS: WATER; JOJOBA OIL

ACTIVE INGREDIENT

Black Soybean Extracts

INACTIVE INGREDIENT

Water
Cocobetain
Cocamidopropyl Betaine
Decyl Glucoside
Sesamum Indicum (Sesame) Seed Extract
Lycium Chinense Fruit Extract
Thunbergii Leaf Extract
Wild Chrysanthemum Extract
Eclipta Prostrata Extract
CACUMEN PLATYCLADI Extract
Cuscutae Semen Extract
Fragaria Ananassa (Strawberry) Fruit Extract
Polygonum Multiflorum Extract
Artemisia Princeps Extract
Cnidium Officinale Rhizome Extract
seaweed Extract
Laminaria Japonica extract
Russian iris extract
Camellia Sinensis Leaf Extract
Panax Ginseng Root Extract
Capsicum Tincture Extract
Jojoba Oil Extract
Salicylic Acid
menthol
Nicotinamide
D-panthenol
Biotin
Polyquat
Rosmarinus
sodium benzoate

PURPOSE

Ciperkey Shampoo removes impurities and dirt that cause hair loss deep into the pores without irritating the skin

Do not use besides the intended use.

If swallowed, consult a physician immediately.

Please keep out of reach of children.

Avoid direct sunlight

Please keep out of reach of children.

INDICATIONS AND USAGE

wet the hair sufficiently with lukewarm water and then use 3cc to clean the scalp, rub it evenly then rinse

Directions

for external use only